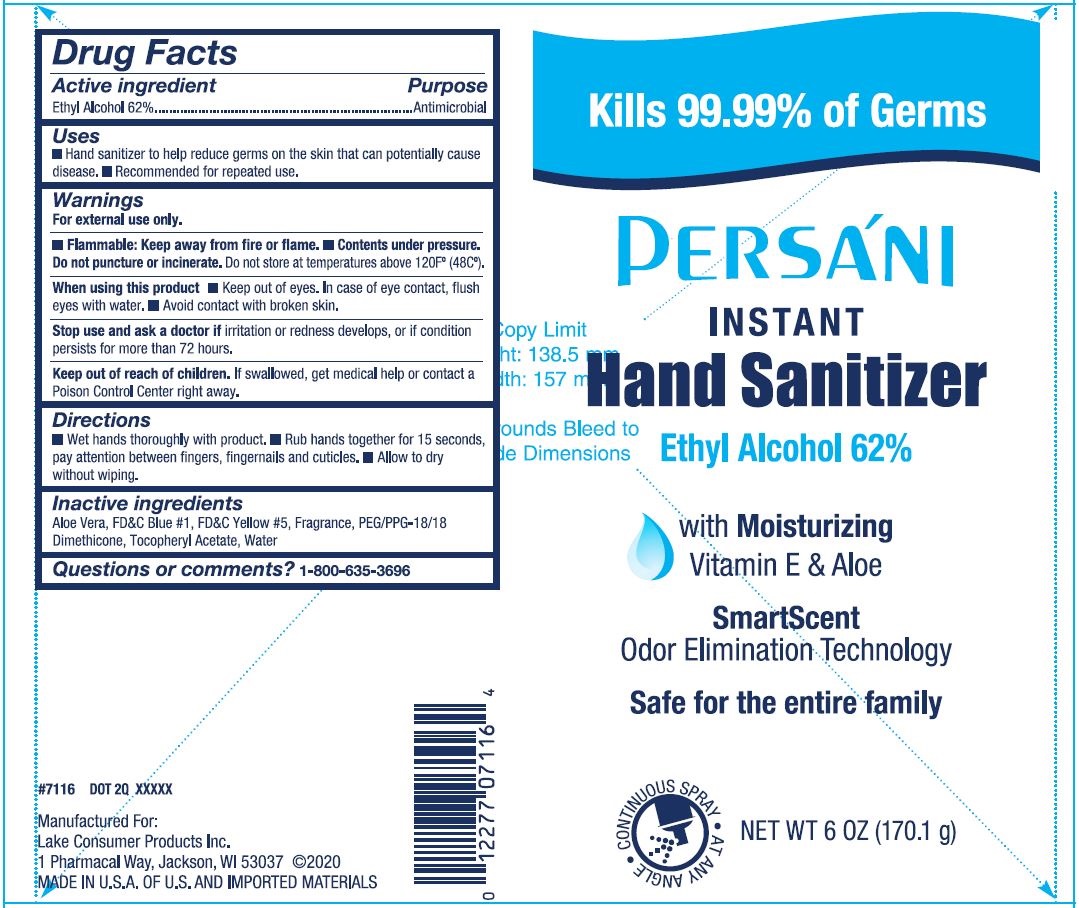 DRUG LABEL: Persani Instant Hand Sanitizer
NDC: 68093-7116 | Form: SPRAY
Manufacturer: Wisconsin Pharmacal Company
Category: otc | Type: HUMAN OTC DRUG LABEL
Date: 20220113

ACTIVE INGREDIENTS: ALCOHOL 0.62 g/1 g
INACTIVE INGREDIENTS: ALOE VERA LEAF; PEG/PPG-18/18 DIMETHICONE; FD&C YELLOW NO. 5; FD&C BLUE NO. 1; ALPHA-TOCOPHEROL ACETATE; WATER

Persani Isntant Hand Sanitizer 6 OZ

Purpose

Hand sanitizer to help reduce germs on the skin that can potentially cause disease.

Drug Facts

Active Ingredient

Active ingredient | Purpose
Ethyl Alcohol 62% | Antimicrobial

Uses

■ Hand sanitizer to help reduce germs on the skin that can potentially cause disease. ■ Recommended for repeated use.

Warnings

For external use only.

OTHER SAFETY INFORMATION

■ Flammable: Keep away from fire or flame. ■ Contents under pressure.
Do not puncture or incinerate. Do not store at temperatures above 120F°(48C°).

When using this product ■ Keep out of eyes. In case of eye contact, flush eyes with water.

■ Avoid contact with broken skin.

Stop use and ask a doctor if irritation or redness develops, or if condition persists for more than 72 hours.

Keep out of reach of children. If swallowed, get medical help or contact a Poison Control Center right away.

Directions

■ Wet hands thoroughly with product. ■ Rub hands together for 15 seconds, pay attention between fingers, fingernails and cuticles. ■ Allow to dry without wiping.

Inactive ingredients

Aloe Vera, FD&C Blue #1, FD&C Yellow #5, Fragrance, PEG/PPG-18/18 Dimethicone, Tocopheryl Acetate, Water

Package Label - Principal Display Panel

Kills 99.99% of Germs

Persani

Instant

Hand Sanitizer

Ethyl Alcohol 62%

with Moisturizing

Vitamin E & Aloe

SmartScent

Odor Eliminination Technology

Safe for the entire family

CONTINUOUS SPRAY

AT ANY ANGLE

NET WT 6 OZ (170.1 g)